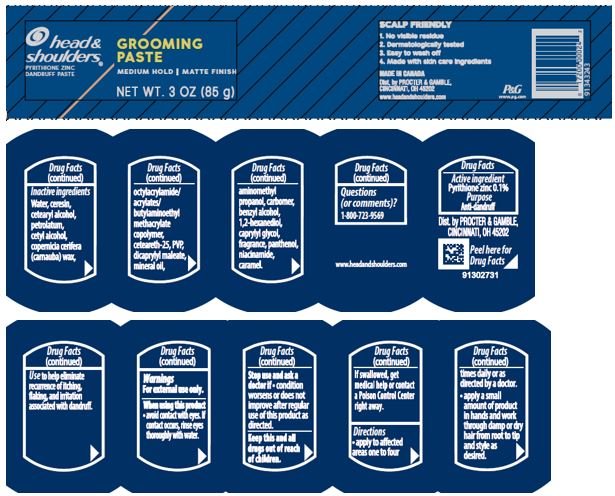 DRUG LABEL: Head and Shoulders Grooming
NDC: 69423-480 | Form: PASTE
Manufacturer: The Procter & Gamble Manufacturing Company
Category: otc | Type: HUMAN OTC DRUG LABEL
Date: 20200721

ACTIVE INGREDIENTS: PYRITHIONE ZINC 0.1 g/100 g
INACTIVE INGREDIENTS: NIACINAMIDE; CARNAUBA WAX; CAPRYLYL GLYCOL; MINERAL OIL; DIOCTYL MALEATE; BENZYL ALCOHOL; 1,2-HEXANEDIOL; PANTHENOL; CETEARETH-25; AMINOMETHYLPROPANOL; POVIDONE K12; CETOSTEARYL ALCOHOL; PETROLATUM; CARBOXYPOLYMETHYLENE; CARAMEL; CERESIN; CETYL ALCOHOL; WATER

Head and Shoulders® Grooming Paste

Drug Facts

Active ingredient

Pyrithione zinc .1%

Purpose

Anti-dandruff

Uses

Use to help eliminate recurrence of itching, flaking, and irritation associated with dandruff.

Warnings

For external use only.

When using this product

- avoid contact with eyes. If contact occurs, rinse eyes thoroughly with water.

Stop use and ask a doctor if

- condition worsens or does not improve after regular use of this product as directed.

KEEP OUT OF REACH OF CHILDREN

Keep this and all drugs out of reach of children. If swallowed, get medical help or contact a Poison Control Center right away.

Directions

- apply to affected areas one to four times daily or as directed by doctor
- apply a small amount of product in hands and work through damp or dry hair from root to tip and style as desired.

Inactive ingredients

Water, ceresin, cetearyl alcohol, petrolatum, cetyl alcohol, copernicia cerifera (carnauba) wax, octylacrylamide/acrylates/butylaminoethyl methacrylate copolymer, ceteareth-25, PVP, dicaprylyl maleate, mineral oil, aminomethyl propanol, carbomer, benzyl alcohol, 1,2-hexanediol, caprylyl glycol, fragrance, panthenol, niacinamide, caramel.

Questions (or comments)?

1-800-723-9569

Dist. by PROCTER & GAMBLE,
CINCINNATI, OH 45202

PRINCIPAL DISPLAY PANEL - 85 g Jar Label

head &
shoulders ®

pyrithione zinc dandruff paste

GROOMING

PASTE

MEDIUM HOLD / MATTE FINISH
NET WT. 3 OZ (85 g)